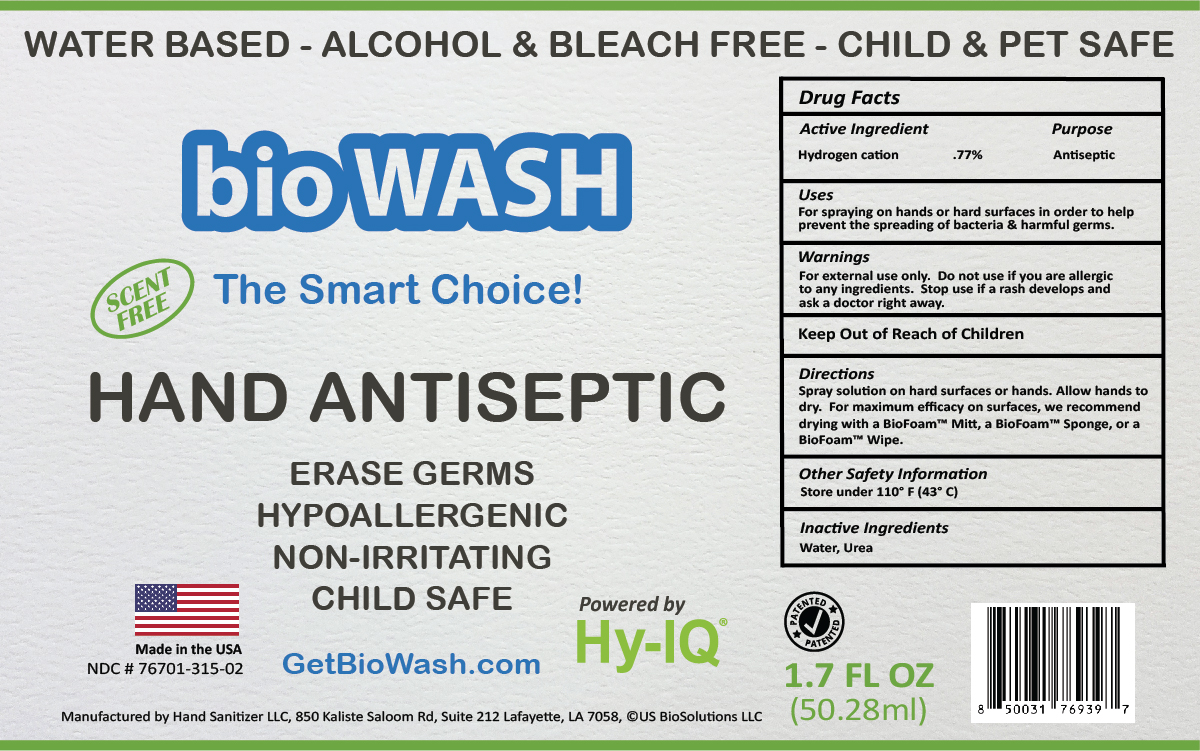 DRUG LABEL: BioWash Hand Antiseptic
NDC: 76701-315 | Form: SPRAY
Manufacturer: Hand Sanitizer LLC
Category: otc | Type: HUMAN OTC DRUG LABEL
Date: 20210820

ACTIVE INGREDIENTS: HYDROGEN CATION 10 mg/1 mL
INACTIVE INGREDIENTS: WATER 940 mg/1 mL; UREA 50 mg/1 mL

Active Ingredient

Hydrogen Cation .77%

Purpose

Antiseptic

Uses

For spraying on hands or hard surfaces in order to help prevent the spreading of bacteria & harmful germs.

Warnings

For external use only. Do not use if you are allergic to any ingredients. Stop use if rash develops and ask a doctor right away.

Keep Out of Reach of Children

Directions

Spray solution on hard surfaces or hands. Allow hands to dry. For maximum efficacy on surfaces, we recommend drying with a BioFoam™ Mitt, a BioFoam™ Sponge, or a BioFoam™ Wipe.

Other Safety Information

Store under 110º F (43º C)

Inactive Ingredients

Water, Urea